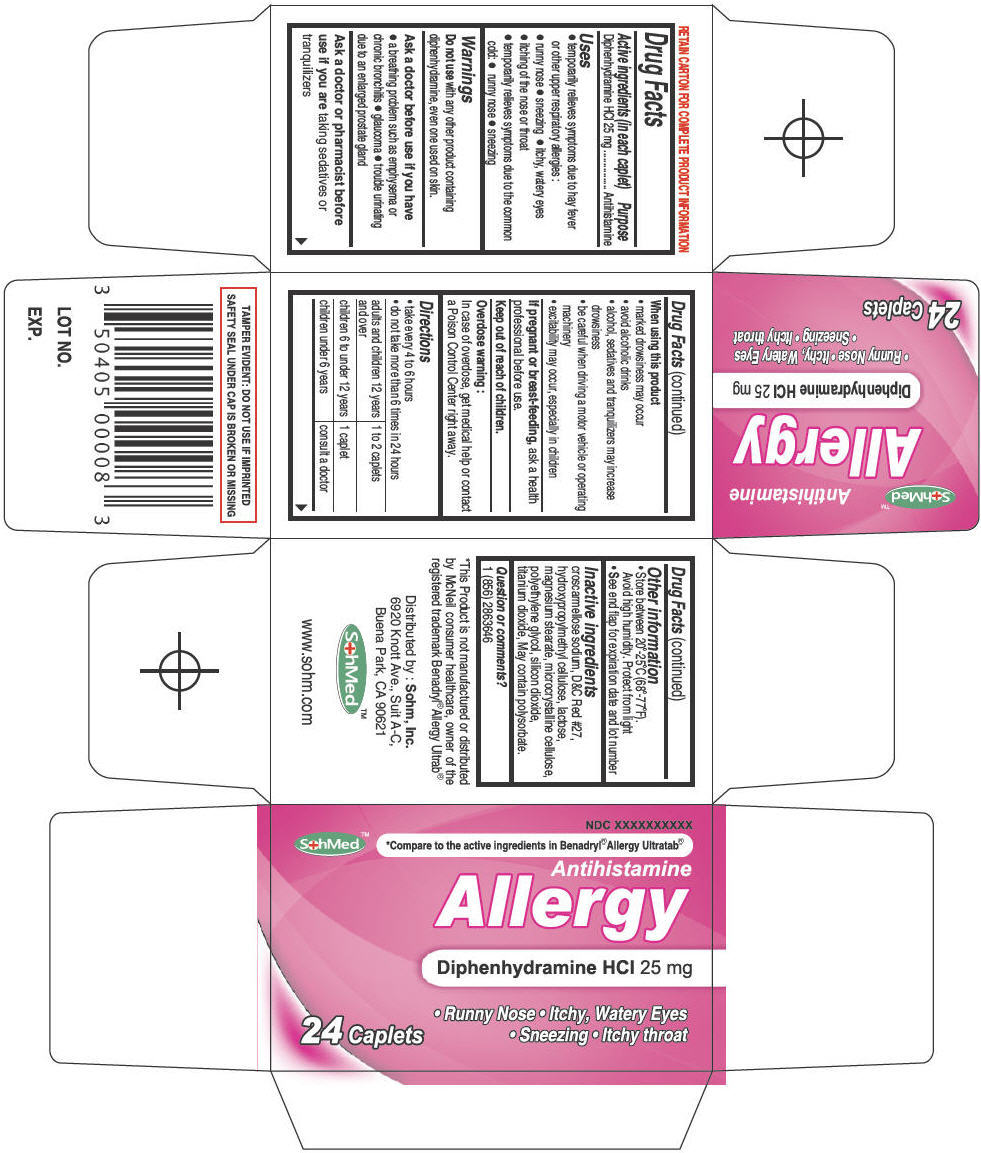 DRUG LABEL: SohMed Allergy
NDC: 50405-004 | Form: TABLET
Manufacturer: SOHM Inc.
Category: otc | Type: HUMAN OTC DRUG LABEL
Date: 20130820

ACTIVE INGREDIENTS: Diphenhydramine Hydrochloride 25 mg/1 1
INACTIVE INGREDIENTS: CROSCARMELLOSE SODIUM; D&C RED NO. 27; HYPROMELLOSES; LACTOSE; MAGNESIUM STEARATE; CELLULOSE, MICROCRYSTALLINE; POLYETHYLENE GLYCOL 6000; SILICON DIOXIDE; TITANIUM DIOXIDE; POLYSORBATE 20

SohMed™ Allergy

Drug Facts

Active ingredients (in each caplet)

Diphenhydramine HCl 25 mg

Purpose

Antihistamine

Uses

- temporarily relieves symptoms due to hay fever or other upper respiratory allergies :
  - runny nose
  - sneezing
  - itchy, watery eyes
  - itching of the nose or throat
- temporarily relieves symptoms due to the common cold:
  - runny nose
  - sneezing

Warnings

Do not use with any other product containing diphenhydramine, even one used on skin.

Ask a doctor before use if you have

- a breathing problem such as emphysema or chronic bronchitis
- glaucoma
- trouble urinating due to an enlarged prostate gland

Ask a doctor or pharmacist before use if you are taking sedatives or tranquilizers

When using this product

- marked drowsiness may occur
- avoid alcoholic drinks
- alcohol, sedatives and tranquilizers may increase drowsiness
- be careful when driving a motor vehicle or operating machinery
- excitability may occur, especially in children

PREGNANCY OR BREAST FEEDING

If pregnant or breast-feeding, ask a health professional before use.

Keep out of reach of children.

Overdose warning

In case of overdose, get medical help or contact a Poison Control Center right away.

Directions

- take every 4 to 6 hours
- do not take more than 6 times in 24 hours

adults and children 12 years and over | 1 to 2 caplets
children 6 to under 12 years | 1 caplet
children under 6 years | consult a doctor

Other information

- Store between 20°-25°C (68°-77°F).
  Avoid high humidity. Protect from light
- See end flap for expiration date and lot number

Inactive ingredients

croscarmellose sodium, D&C Red #27, hydroxypropylmethyl cellulose, lactose, magnesium stearate, microcrystalline cellulose, polyethylene glycol, silicon dioxide, titanium dioxide, May contain polysorbate.

Question or comments?

1 (856) 2863646

Distributed by : Sohm, Inc.
6920 Knott Ave., Suit A-C,
Buena Park, CA 90621

PRINCIPAL DISPLAY PANEL - 24 Caplet Bottle Carton

NDC XXXXXXXXXX

SohMed™
*Compare to the active ingredients in Benadryl® Allergy Ultratab®

Antihistamine

Allergy

Diphenhydramine HCl 25 mg

24 Caplets

• Runny Nose • Itchy, Watery Eyes
• Sneezing • Itchy throat